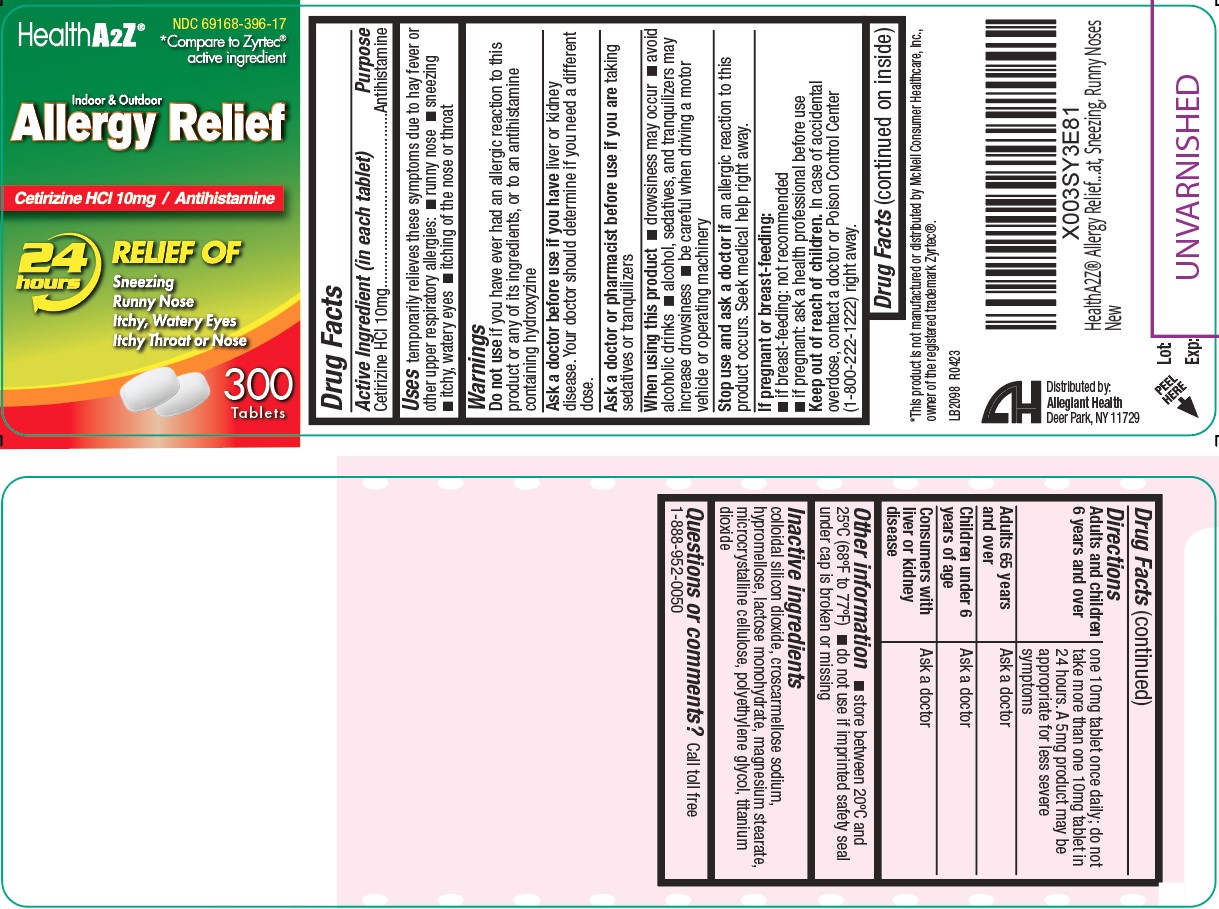 DRUG LABEL: Allergy Relief
NDC: 69168-396 | Form: TABLET
Manufacturer: Allegiant Health
Category: otc | Type: HUMAN OTC DRUG LABEL
Date: 20191212

ACTIVE INGREDIENTS: CETIRIZINE HYDROCHLORIDE 10 mg/1 1
INACTIVE INGREDIENTS: MAGNESIUM STEARATE; CELLULOSE, MICROCRYSTALLINE; POLYETHYLENE GLYCOL, UNSPECIFIED; TITANIUM DIOXIDE; SILICON DIOXIDE; CROSCARMELLOSE SODIUM; HYPROMELLOSES; LACTOSE MONOHYDRATE

Drug Facts

Active ingredient (in each tablet)

Cetirizine HCl 10 mg

Purpose

Antihistamine

Uses

temporarily relieves these symptoms due to hay fever or other upper respiratory allergies:

- runny nose
- sneezing
- itchy, watery eyes
- itching of the nose or throat

Warnings

Do not use if you have ever had an allergic reaction to this product or any of its ingredients or to an antihistamine containing hydroxyzine

Ask doctor if you have

- liver or kidney disease. Your doctor should determine if you need a different dose.

Ask doctor or pharmacist before use if you are

taking sedatives or tranquilizers

When using this product

- drowsiness may occur
- avoid alcoholic drinks
- alcohol, sedatives, and tranquilizers may increase drowsiness
- be careful when driving a motor vehicle or operating machinery

Stop use and ask doctor

if an allergic reaction to this product occurs. Seek medical help right away.

If pregnant or breast-feeding, ask a health professional before use.

Keep out of reach of children

In case of accidental overdose, contact a octor or Poison Control Center (1-800-222-1222) right away.

Directions

- Adults and children 6 years and over: one 10mg tablet once daily; do not take more than one 10mg tablet in 24 hours. A 5mg product may be appropriate for less severe symptoms
- Adults 65 years and over: ask a doctor
- Children under 6 years of age: ask a doctor
- Consumers with liver or kidney disease: ask a doctor

Other information

- store between 20°C to 25°C (68°F to 77°F)
- do not use ifimprinted safety seal under cap is broken or missing

Inactive Ingredients

colloidal silicon dioxide, croscarmellose sodium, hypromellose, lactose monohydrate, magnesium stearate, microcrystalline cellulose, polyethylene glycol, titanium dioxide

Package/Label Principal Display Panel

Allergy Relief